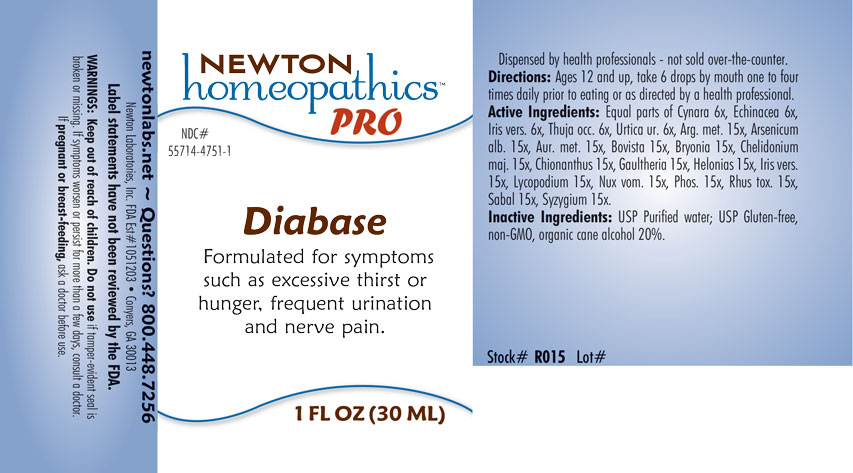 DRUG LABEL: Diabase
NDC: 55714-4751 | Form: LIQUID
Manufacturer: Newton Laboratories, Inc.
Category: homeopathic | Type: HUMAN OTC DRUG LABEL
Date: 20201202

ACTIVE INGREDIENTS: PHOSPHORUS 15 [hp_X]/1 mL; TOXICODENDRON PUBESCENS LEAF 15 [hp_X]/1 mL; THUJA OCCIDENTALIS LEAFY TWIG 6 [hp_X]/1 mL; SILVER 15 [hp_X]/1 mL; SAW PALMETTO 15 [hp_X]/1 mL; GOLD 15 [hp_X]/1 mL; IRIS VERSICOLOR ROOT 15 [hp_X]/1 mL; STRYCHNOS NUX-VOMICA SEED 15 [hp_X]/1 mL; ECHINACEA, UNSPECIFIED 6 [hp_X]/1 mL; LYCOPERDON UTRIFORME FRUITING BODY 15 [hp_X]/1 mL; GAULTHERIA PROCUMBENS TOP 15 [hp_X]/1 mL; SYZYGIUM CUMINI SEED 15 [hp_X]/1 mL; CHIONANTHUS VIRGINICUS BARK 15 [hp_X]/1 mL; CHAMAELIRIUM LUTEUM ROOT 15 [hp_X]/1 mL; ARSENIC TRIOXIDE 15 [hp_X]/1 mL; LYCOPODIUM CLAVATUM SPORE 15 [hp_X]/1 mL; CYNARA SCOLYMUS LEAF 6 [hp_X]/1 mL; URTICA URENS 6 [hp_X]/1 mL; BRYONIA ALBA ROOT 15 [hp_X]/1 mL; CHELIDONIUM MAJUS 15 [hp_X]/1 mL
INACTIVE INGREDIENTS: WATER; ALCOHOL

Diabase 4751L

INDICATIONS & USAGE SECTION

Formulated for symptoms such as excessive thirst or hunger, frequent urination and nerve pain.

DOSAGE & ADMINISTRATION SECTION

Directions: Ages 12 and up, take 6 drops by mouth (ages 0 to 11, give 3 drops) one to four times daily or as directed by a health professional.

OTC - ACTIVE INGREDIENT SECTION

Equal parts of Cynara 6x, Echinacea 6x, Iris vers. 6x, Thuja occ. 6x, Urtica ur. 15x, Arg. met. 15x, Arsenicum alb. 15x, Aur. met. 15x, Bovista 15x, Bryonia 15x, Chelidonium maj. 15x, Chionanthus 15x, Gaultheria 15x, Helonias 15x, Iris vers. 15x, Lycopodium 15x, Nux vom. 15x, Phos. 15x, Rhus tox. 15x, Sabal 15x, Syzygium 15x.

OTC - PURPOSE SECTION

Formulated for symptoms such as excessive thirst or hunger, frequent urination and nerve pain.

INACTIVE INGREDIENT SECTION

Inactive Ingredients: USP Purified water; USP Gluten-free, non-GMO, organic cane alcohol 20%.

OTC - QUESTIONS SECTION

newtonlabs.net - Questions? 800.448.7256

Newton Laboratories, Inc. FDA Est # 1051203 Conyers, GA 30013

WARNINGS SECTION

WARNINGS: Keep out of reach of children. Do not use if tamper-evident seal is broken or missing. If symptoms worsen or persist for more than a few days, consult a doctor. If pregnant or breast-feeding, ask a doctor before use.

OTC - PREGNANCY OR BREAST FEEDING SECTION

If pregnant or breast-feeding, ask a doctor before use.

OTC - KEEP OUT OF REACH OF CHILDREN SECTION

Keep out of reach of children.